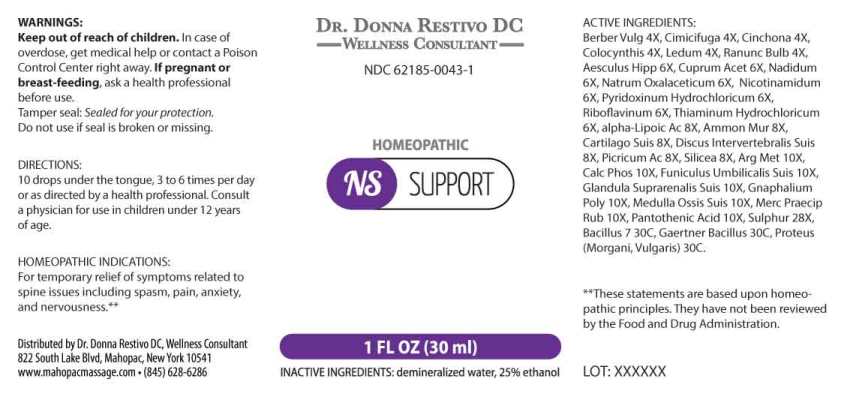 DRUG LABEL: NS Support
NDC: 62185-0043 | Form: LIQUID
Manufacturer: Dr. Donna Restivo DC
Category: homeopathic | Type: HUMAN OTC DRUG LABEL
Date: 20230315

ACTIVE INGREDIENTS: BERBERIS VULGARIS ROOT BARK 4 [hp_X]/1 mL; BLACK COHOSH 4 [hp_X]/1 mL; CINCHONA OFFICINALIS BARK 4 [hp_X]/1 mL; CITRULLUS COLOCYNTHIS FRUIT PULP 4 [hp_X]/1 mL; LEDUM PALUSTRE TWIG 4 [hp_X]/1 mL; RANUNCULUS BULBOSUS 4 [hp_X]/1 mL; HORSE CHESTNUT 6 [hp_X]/1 mL; CUPRIC ACETATE 6 [hp_X]/1 mL; NADIDE 6 [hp_X]/1 mL; SODIUM DIETHYL OXALACETATE 6 [hp_X]/1 mL; NIACINAMIDE 6 [hp_X]/1 mL; PYRIDOXINE HYDROCHLORIDE 6 [hp_X]/1 mL; RIBOFLAVIN 6 [hp_X]/1 mL; THIAMINE HYDROCHLORIDE 6 [hp_X]/1 mL; THIOCTIC ACID 8 [hp_X]/1 mL; AMMONIUM CHLORIDE 8 [hp_X]/1 mL; SUS SCROFA CARTILAGE 8 [hp_X]/1 mL; SUS SCROFA INTERVERTEBRAL DISC 8 [hp_X]/1 mL; PICRIC ACID 8 [hp_X]/1 mL; SILICON DIOXIDE 8 [hp_X]/1 mL; SILVER 10 [hp_X]/1 mL; TRIBASIC CALCIUM PHOSPHATE 10 [hp_X]/1 mL; SUS SCROFA UMBILICAL CORD 10 [hp_X]/1 mL; SUS SCROFA ADRENAL GLAND 10 [hp_X]/1 mL; PSEUDOGNAPHALIUM OBTUSIFOLIUM 10 [hp_X]/1 mL; SUS SCROFA BONE MARROW 10 [hp_X]/1 mL; MERCURIC OXIDE 10 [hp_X]/1 mL; PANTOTHENIC ACID 10 [hp_X]/1 mL; SULFUR 28 [hp_X]/1 mL; ENTEROBACTER CLOACAE 30 [hp_C]/1 mL; SALMONELLA ENTERICA SUBSP. ENTERICA SEROVAR ENTERITIDIS 30 [hp_C]/1 mL; PROTEUS MORGANII 30 [hp_C]/1 mL; PROTEUS VULGARIS 30 [hp_C]/1 mL
INACTIVE INGREDIENTS: WATER; ALCOHOL

Drug Facts:

ACTIVE INGREDIENTS:

Berberis Vulgaris 4X, Cimicifuga Racemosa 4X, Cinchona Officinalis 4X, Colocynthis 4X, Ledum Palustre 4X, Ranunculus Bulbosus 4X, Aesculus Hippocastanum 6X, Cuprum Aceticum 6X, Nadidum 6X, Natrum Oxalaceticum 6X, Nicotinamidum 6X, Pyridoxinum Hydrochloricum 6X, Riboflavinum 6X, Thiaminum Hydrochloricum 6X, alpha-Lipoicum Acidum 8X, Ammonium Muriaticum 8X, Cartilago Suis 8X, Discus Intervertebralis Suis 8X, Picricum Acidum 8X, Silicea 8X, Argentum Metallicum 10X, Calcarea Phosphorica 10X, Funiculus Umbilicalis Suis 10X, Glandula Suprarenalis Suis 10X, Gnaphalium Polycephalum 10X, Medulla Ossis Suis 10X, Mercurius Praecipitatus Ruber 10X, Pantothenic Acid 10X, Sulphur 28X, Bacillus 7 (Enterobacter Cloacae) 30C, Gaertner Bacillus (Bach) 30C, Proteus (Morgani) 30C, Proteus (Vulgaris) 30C.

HOMEOPATHIC INDICATIONS:

For temporary relief of symptoms related to spine issues including spasm, pain, anxiety, and nervousness.**

**These statements are based upon homeopathic principles. They have not been reviewed by the Food and Drug Administration.

WARNINGS:

Keep out of reach of children. In case of overdose, get medical help or contact or a Poison Control Center right away.

If pregnant or breast-feeding, ask a health professional before use.

Tamper seal: "Sealed for Your Protection."

Do not use if seal is broken or missing.

Keep out of reach of children. In case of overdose, get medical help or contact or a Poison Control Center right away.

DIRECTIONS:

10 drops under the tongue, 3 to 6 times per day or as directed by a health professional. Consult a physician for use in children under 12 years of age.

HOMEOPATHIC INDICATIONS:

For temporary relief of symptoms related to spine issues including spasm, pain, anxiety, and nervousness.**

**These statements are based upon traditional homeopathic principles. They have not been reviewed by the Food and Drug Administration.

INACTIVE INGREDIENTS:

demineralized water, 25% ethanol

QUESTIONS:

Distributed by Dr. Donna Restivo DC, Wellness Consultant
822 South Lake Blvd, Mahopac, New York 10541
www.mahopacmassage.com • (845) 628-6286

PACKAGE LABE DISPLAY:

DR. DONNA RESTIVO DC

WELLNESS CONSULTANT

NDC 62185-0043-1

HOMEOPATHIC

NS SUPPORT

1 FL OZ (30 ml)